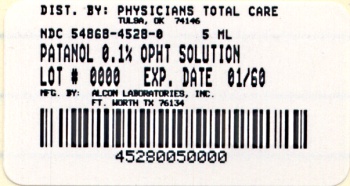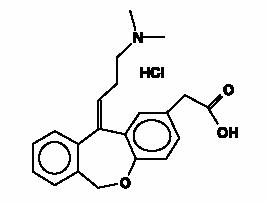 DRUG LABEL: PATANOL
NDC: 54868-4528 | Form: SOLUTION/ DROPS
Manufacturer: Physicians Total Care, Inc.
Category: prescription | Type: HUMAN PRESCRIPTION DRUG LABEL
Date: 20110512
DEA Schedule: CV

ACTIVE INGREDIENTS: OLOPATADINE HYDROCHLORIDE 1 mg/1 mL
INACTIVE INGREDIENTS: BENZALKONIUM CHLORIDE; SODIUM PHOSPHATE, DIBASIC; SODIUM CHLORIDE; HYDROCHLORIC ACID; SODIUM HYDROXIDE; WATER

DESCRIPTION

PATANOL® (olopatadine hydrochloride ophthalmic solution) 0.1% is a sterile ophthalmic solution containing olopatadine, a relatively selective H1-receptor antagonist and inhibitor of histamine release from the mast cell for topical administration to the eyes. Olopatadine hydrochloride is a white, crystalline, water-soluble powder with a molecular weight of 373.88. The chemical structure is presented below:

Chemical Name:11-[(Z)-3-(Dimethylamino)propylidene]-6-11-dihydrodibenz[b,e]oxepin-2-acetic acid hydrochloride.

Each mL of PATANOL contains: Active: 1.11 mg olopatadine hydrochloride equivalent to 1 mg olopatadine. Preservative: benzalkonium chloride 0.01%. Inactives: dibasic sodium phosphate; sodium chloride; hydrochloric acid/sodium hydroxide (adjust pH); and purified water. It has a pH of approximately 7 and an osmolality of approximately 300 mOsm/kg.

CLINICAL PHARMACOLOGY

Olopatadine is an inhibitor of the release of histamine from the mast cell and a relatively selective histamine H1-antagonist that inhibits the in vivo and in vitro type 1 immediate hypersensitivity reaction including inhibition of histamine induced effects on human conjunctival epithelial cells. Olopatadine is devoid of effects on alpha-adrenergic, dopamine, and muscarinic type 1 and 2 receptors. Following topical ocular administration in man, olopatadine was shown to have low systemic exposure. Two studies in normal volunteers (totaling 24 subjects) dosed bilaterally with olopatadine 0.15% ophthalmic solution once every 12 hours for 2 weeks demonstrated plasma concentrations to be generally below the quantitation limit of the assay (<0.5 ng/mL). Samples in which olopatadine was quantifiable were typically found within 2 hours of dosing and ranged from 0.5 to 1.3 ng/mL. The half-life in plasma was approximately 3 hours, and elimination was predominantly through renal excretion. Approximately 60-70% of the dose was recovered in the urine as parent drug. Two metabolites, the mono-desmethyl and the N-oxide, were detected at low concentrations in the urine.

Results from an environmental study demonstrated that PATANOL was effective in the treatment of the signs and symptoms of allergic conjunctivitis when dosed twice daily for up to 6 weeks. Results from conjunctival antigen challenge studies demonstrated that PATANOL, when subjects were challenged with antigen both initially and up to 8 hours after dosing, was significantly more effective than its vehicle in preventing ocular itching associated with allergic conjunctivitis.

INDICATIONS AND USAGE

PATANOL (olopatadine hydrochloride ophthalmic solution) 0.1% is indicated for the treatment of the signs and symptoms of allergic conjunctivitis.

CONTRAINDICATIONS

PATANOL (olopatadine hydrochloride ophthalmic solution) 0.1% is contraindicated in persons with a known hypersensitivity to olopatadine hydrochloride or any components of PATANOL.

WARNINGS

PATANOL (olopatadine hydrochloride ophthalmic solution) 0.1% is for topical use only and not for injection or oral use.

PRECAUTIONS

Information for Patients

To prevent contaminating the dropper tip and solution, care should be taken not to touch the eyelids or surrounding areas with the dropper tip of the bottle. Keep bottle tightly closed when not in use.

Patients should be advised not to wear a contact lens if their eye is red. PATANOL® should not be used to treat contact lens-related irritation. The preservative in PATANOL, benzalkonium chloride, may be absorbed by soft contact lenses. Patients who wear soft contact lenses and whose eyes are not red should be instructed to wait at least ten minutes after instilling PATANOL (olopatadine hydrochloride ophthalmic solution) 0.1% before they insert their contact lenses.

Carcinogenesis, Mutagenesis, Impairment of Fertility

Olopatadine administered orally was not carcinogenic in mice and rats in doses up to 500mg/kg/day and 200mg/kg/day, respectively. Based on a 40 µl drop size, these doses were 78,125 and 31,250 times higher than the maximum recommended ocular human dose (MROHD). No mutagenic potential was observed when olopatadine was tested in an in vitro bacterial reverse mutation (Ames) test, an in vitro mammalian chromosome aberration assay or an in vivo mouse micronucleus test. Olopatadine administered to male and female rats at oral doses of 62,500 times MROHD level resulted in a slight decrease in the fertility index and reduced implantation rate; no effects on reproductive function were observed at doses of 7,800 times the maximum recommended ocular human use level.

Pregnancy

Pregnancy Category C. Olopatadine was found not to be teratogenic in rats and rabbits. However, rats treated at 600 mg/kg/day, or 93,750 times the MROHD and rabbits treated at 400 mg/kg/day, or 62,500 times the MROHD, during organogenesis showed a decrease in live fetuses. There are, however, no adequate and well-controlled studies in pregnant women. Because animal studies are not always predictive of human responses, this drug should be used in pregnant women only if the potential benefit to the mother justifies the potential risk to the embryo or fetus.

Nursing Mothers

Olopatadine has been identified in the milk of nursing rats following oral administration. It is not known whether topical ocular administration could result in sufficient systemic absorption to produce detectable quantities in the human breast milk. Nevertheless, caution should be exercised when PATANOL (olopatadine hydrochloride ophthalmic solution) 0.1% is administered to a nursing mother.

Pediatric Use

Safety and effectiveness in pediatric patients below the age of 3 years have not been established.

Geriatric Use

No overall differences in safety or effectiveness have been observed between elderly and younger patients.

ADVERSE REACTIONS

Headaches have been reported at an incidence of 7%. The following adverse experiences have been reported in less than 5% of patients: asthenia, blurred vision, burning or stinging, cold syndrome, dry eye, foreign body sensation, hyperemia, hypersensitivity, keratitis, lid edema, nausea, pharyngitis, pruritus, rhinitis, sinusitis, and taste perversion. Some of these events were similar to the underlying disease being studied.

DOSAGE AND ADMINISTRATION

The recommended dose is one drop in each affected eye two times per day at an interval of 6 to 8 hours.

HOW SUPPLIED

PATANOL (olopatadine hydrochloride ophthalmic solution) 0.1% is supplied as follows: 5 mL in plastic DROP-TAINER® dispenser.

5 mL: NDC 54868-4528-0

Storage

Store at 39°F-77°F (4°C-25°C).

Rx Only

U.S. Patent Nos. 4,871,865; 4,923,892; 5,116,863; 5,641,805.

© 2000, 2003, 2005 Alcon, Inc.

ALCON LABORATORIES, INC.
Fort Worth, Texas 76134 USA

Printed in USA

Relabeling of "Additional" label by:
Physicians Total Care, Inc.
Tulsa, OK 74146

PRINCIPAL DISPLAY PANEL

PATANOL (olopatadine hydrochloride ophthalmic solution) 0.1%

5 mL

NDC 54868-4528-0